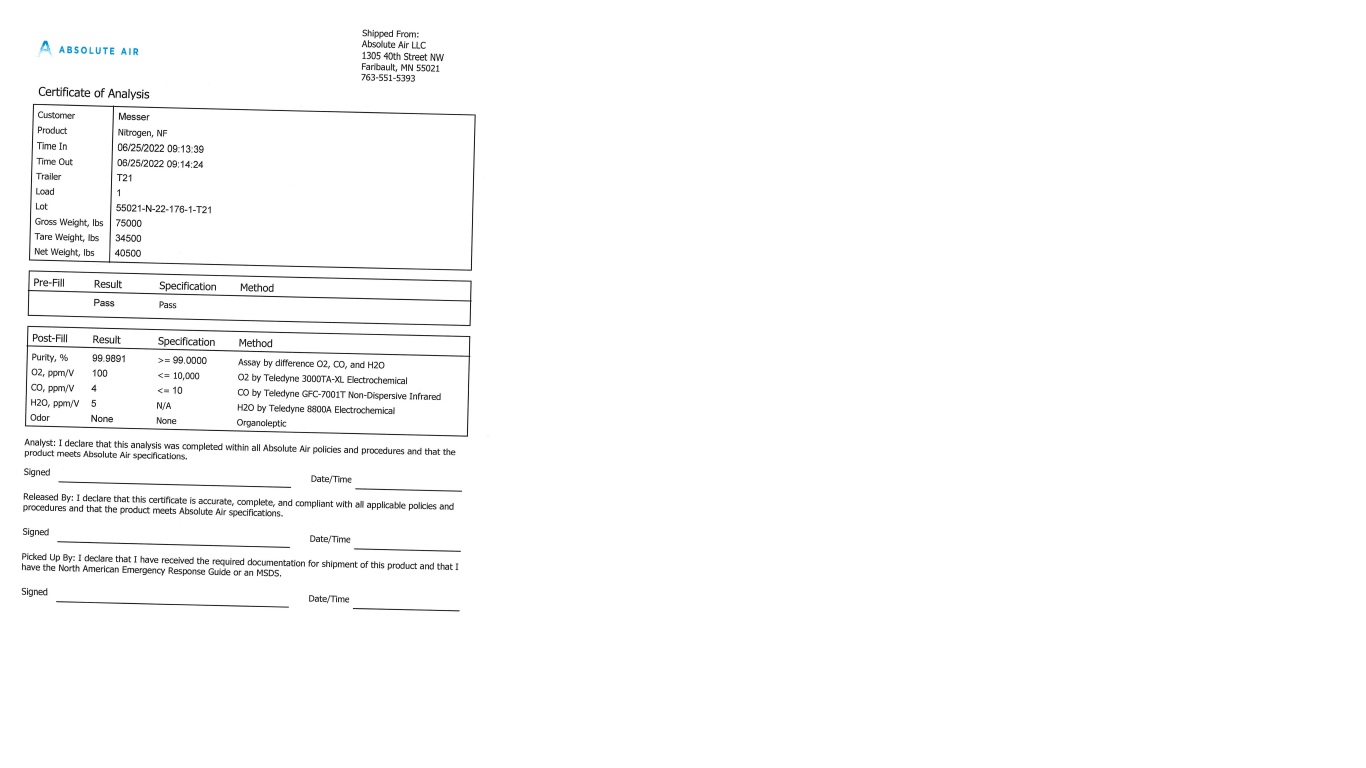 DRUG LABEL: Nitrogen
NDC: 82666-002 | Form: GAS
Manufacturer: ABSOLUTE AIR LLC
Category: prescription | Type: HUMAN PRESCRIPTION DRUG LABEL
Date: 20251208

ACTIVE INGREDIENTS: NITROGEN 999 mL/1 L

Nitrogen

PACKAGE LABEL

ABSOLUTE AIR Shipped From:

Absolute Air LLC

1305 40th Street NW

Faribault, MN 55021

763-551-5393

Certificate of Analysis

Customer Messer

Product Nitrogen, NF

Time In 06/25/2022 09:13:39

Time Out 06/25/2022 09:14:24

Trailer T21

Load 1

Lot 55021-N-22-176-1-T21

Gross Weight, lbs 75000

Tare Weight, lbs 34500

Net Weight, lbs 40500

Pre-Fill Result Specification Method

Pass Pass

Post-Fill Result Specification Method

Purity, % 99.9891 >= 99.0000 Assay by difference O2, CO, and H2O

O2, ppm/V 100 <= 10,000 O2 by Teledyne 3000TA-XL Electrochemical

CO, ppm/V 4 <= 10 CO by Teledyne GFC-7001T Non-Dispersive Infrared

H2O, ppm/V 5 N/A H2O by Teledyne 8800A Electrochemical

Odor None None Organoleptic

Analyst: I declare that this analysis was completed within all Absolute Air policies and procedures and that the product meets Absolute Air specifications.

Signed Date/Time

Release By: I declare that this certificate is accurate, completed, and compliant with the applicable policies and procedures and that the product meets Absolute Air specifications.

Signed Date/Time

Picked Up By: I declare that I have received the required documentation for shipment of this product and that I have the North American Emergency Response Guide or an MSDS.

Signed Date/Time